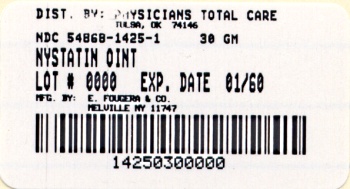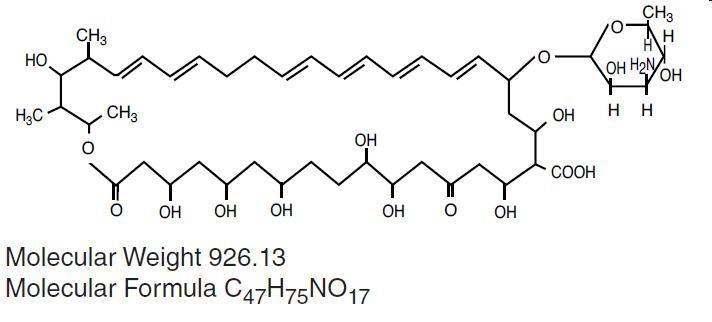 DRUG LABEL: Nystatin
NDC: 54868-1425 | Form: OINTMENT
Manufacturer: Physicians Total Care, Inc.
Category: prescription | Type: HUMAN PRESCRIPTION DRUG LABEL
Date: 20120906

ACTIVE INGREDIENTS: nystatin 100000 [USP'U]/1 g
INACTIVE INGREDIENTS: HIGH DENSITY POLYETHYLENE; Mineral Oil

NYSTATIN OINTMENT USP

Rx only

DESCRIPTION

Nystatin Ointment USP, for topical use only, contains 100,000 USP Nystatin Units per gram, in a polyethylene and mineral oil base. The structural formula is as follows:

CLINICAL PHARMACOLOGY

Nystatin is an antifungal antibiotic which is both fungistatic and fungicidal in vitro against a wide variety of yeasts and yeast-like fungi. It probably acts by binding to sterols in the cell membrane of the fungus with a resultant change in membrane permeability allowing leakage of intracellular components. Nystatin is a polyene antibiotic that is obtained from Streptomyces noursei, and is the first well tolerated antifungal antibiotic of dependable efficacy for the treatment of cutaneous, oral and intestinal infections caused by Candida [Monilia]albicans and other Candida species. It exhibits no appreciable activity against bacteria.

Nystatin provides specific therapy for all localized forms of candidiasis. Symptomatic relief is rapid, often occurring within 24 to 72 hours after the initiation of treatment. Cure is effected both clinically and mycologically in most cases of localized candidiasis.

INDICATIONS AND USAGE

Nystatin Ointment is indicated in the treatment of cutaneous or mucocutaneous mycotic infections caused by Candida [Monilia]albicans and other Candida species.

CONTRAINDICATIONS

Nystatin Ointment is contraindicated in patients with a history of hypersensitivity to any of its components.

PRECAUTIONS

Should a reaction of hypersensitivity occur the drug should be immediately withdrawn and appropriate measures taken.

This preparation is not for ophthalmic use.

ADVERSE REACTIONS

Nystatin is virtually non-toxic and nonsensitizing and is well tolerated by all age groups including debilitated infants, even on prolonged administration. If irritation on topical application should occur, discontinue medication.

DOSAGE AND ADMINISTRATION

Nystatin Ointment should be applied liberally to affected areas twice a day or as indicated until healing is complete. Nystatin cream is usually preferred to nystatin ointment in candidiasis involving intertriginous areas; very moist lesions, however, are best treated with nystatin topical powder.

This preparation does not stain skin or mucous membranes and provides a simple, convenient means of treatment.

HOW SUPPLIED

Nystatin Ointment (100,000 USP Nystatin Units per gram) is a yellow ointment available as follows:

NDC 54868-1425-0 15 gram tube

NDC 54868-1425-1 30 gram tube

Store at controlled room temperature 15°- 30°C (59°-86°F).

E. FOUGERA & CO.
A division of Fougera Pharmaceuticals Inc.
Melville, New York 11747
I20715H
R08/11
#21

Additional barcode labeling by:

Physicians Total Care, Inc.

Tulsa, Oklahoma 74146

PACKAGE LABEL – PRINCIPAL DISPLAY PANEL

NDC 54868-1425-1

Rx only

NYSTATIN OINTMENT USP

100,000 USP Nystatin Units Per Gram

WARNING: Keep this and all

drugs out of reach of children.

For Topical Use Only.

Not for Ophthalmic Use.

NET WT 30 grams